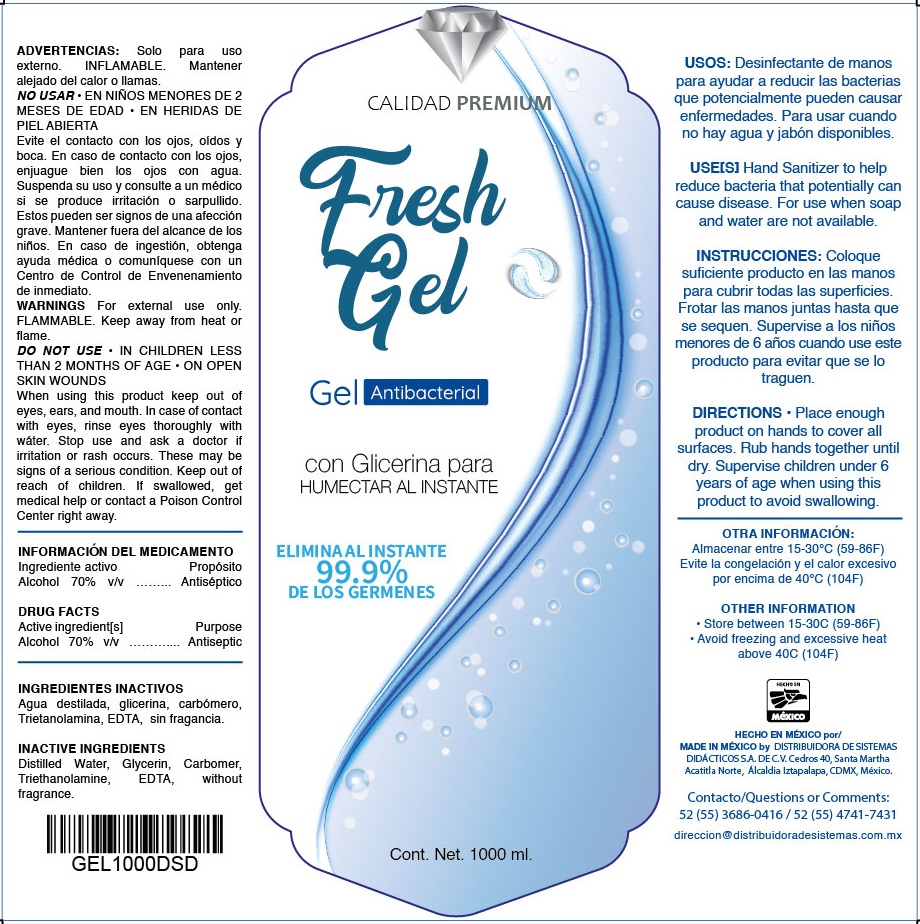 DRUG LABEL: Calidad Premium Fresh Antibacterial
NDC: 79728-000 | Form: GEL
Manufacturer: Distribuidora de Sistemas Didacticos , S.A. de C.V.
Category: otc | Type: HUMAN OTC DRUG LABEL
Date: 20220914

ACTIVE INGREDIENTS: ALCOHOL 0.7 mL/1 mL
INACTIVE INGREDIENTS: WATER; GLYCERIN; CARBOMER HOMOPOLYMER, UNSPECIFIED TYPE; TROLAMINE; EDETIC ACID

Calidad Premium Fresh Gel Antibacterial

Active ingredient[s]

Alcohol 70% v/v

Purpose

Antiseptic

INACTIVE INGREDIENTS

Distilled Water, Glycerin, Carbomer, Triethanolamine, EDTA, Without fragrance.

USE[S]

Hand Sanitizer to help reduce bacteria that potentially can cause disease. For use when soap and water are not available.

WARNINGS

For external use only. FLAMMABLE. Keep away from heat or flame.

DO NOT USE

- IN CHILDREN LESS THAN 2 MONTHS OF AGE
- ON OPEN SKIN WOUNDS

When using this product

keep out of eyes, ears, and mouth. In case of contact with eyes, rinse eyes thoroughly with water.

Stop use and ask a doctor

if irritation or rash occurs. These may be signs of a serious condition.

Keep out of reach of children.

If swallowed, get medical help or contact a Poison Control Center right away.

DIRECTIONS

Place enough product on hands to cover all surfaces. Rub hands together until dry. Supervise children under 6 years of age when using this product to avoid swallowing.

OTHER INFORMATION

- Store between 15-30C (59-86F)
- Avoid freezing and excessive heat above 40C (104F)

Questions or Comments:

52 (55) 3686-0416 / 52 (55) 4741-7431 direccion@distribuidoradesistemas.com.mx